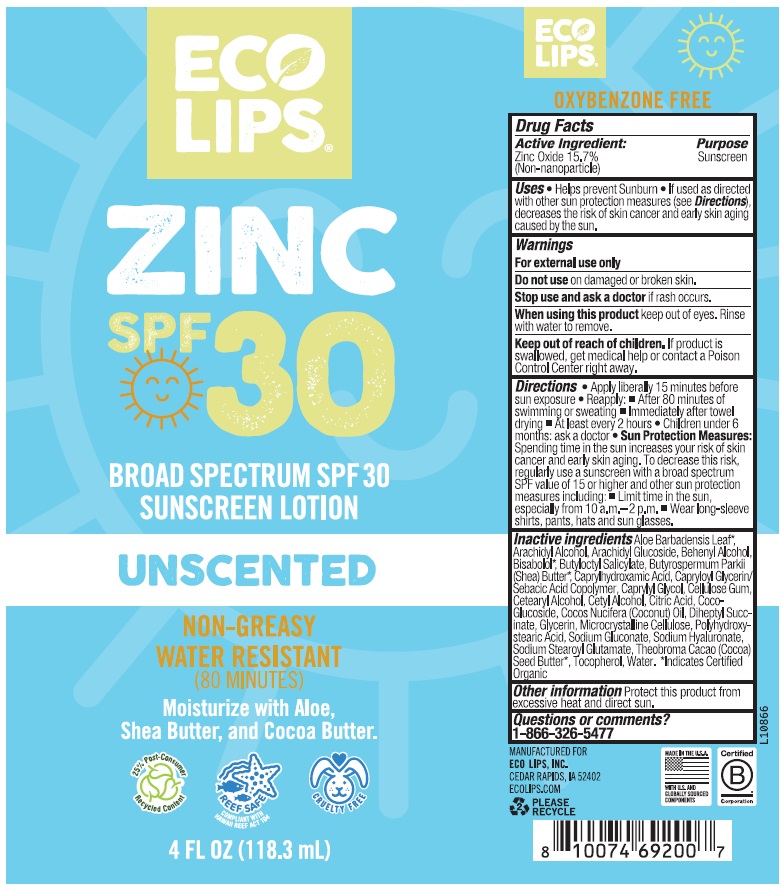 DRUG LABEL: Eco Lips Zinc SPF 30 Broad Spectrum Sunscreen Unscented
NDC: 75071-415 | Form: LOTION
Manufacturer: Eco Lips, Inc.
Category: otc | Type: HUMAN OTC DRUG LABEL
Date: 20250108

ACTIVE INGREDIENTS: ZINC OXIDE 15.7 g/100 mL
INACTIVE INGREDIENTS: COCONUT OIL; GLYCERIN; CAPRYLYL GLYCOL; CITRIC ACID MONOHYDRATE; ALOE VERA LEAF; CAPRYLOYL GLYCERIN/SEBACIC ACID COPOLYMER (2000 MPA.S); CETYL ALCOHOL; BUTYLOCTYL SALICYLATE; SHEA BUTTER; CETOSTEARYL ALCOHOL; SODIUM STEAROYL GLUTAMATE; COCOA BUTTER; MICROCRYSTALLINE CELLULOSE; CAPRYLHYDROXAMIC ACID; COCO GLUCOSIDE; DIHEPTYL SUCCINATE; POLYHYDROXYSTEARIC ACID (2300 MW); SODIUM GLUCONATE; HYALURONATE SODIUM; TOCOPHEROL; WATER; ARACHIDYL ALCOHOL; ARACHIDYL GLUCOSIDE; DOCOSANOL; LEVOMENOL; CARBOXYMETHYLCELLULOSE SODIUM, UNSPECIFIED

Eco Lips Zinc SPF 30 Sunscreen Lotion Unscented 4 oz tube

Active Ingredient

Active Ingredient: Zinc Oxide - 15.7% (non-nanoparticle)

Purpose

Purpose Sunscreen

Uses

• Helps prevent sunburn
• If used as directed with other sun protection measures (see Directions), decreases the risk of skin cancer and early skin aging caused by the sun.

Warnings

Warnings For external use only

Do not use on damaged or broken skin.

Stop use and ask a doctor if rash occurs.

When using this product keep out of eyes. Rinse with water to remove.

Keep out of reach of children.If swallowed, get medical help or contact a Poison Control Center right away.

Directions

•Apply liberally 15 minutes before sun exposure.

• Reapply: • After 80 minutes of swimming or sweating. • Immediately after towel drying. • At least every 2 hours.

• Children under six months: Ask a doctor.
• Sun Protection Measures:Spending time in the sun increases your risk of skin cancer and early skin aging. To decrease this risk, regularly use a sunscreen with a Broad Spectrum SPF value of 15 or higher and other sun protection measures including: • Limit time in the sun especially from 10 a.m. – 2 p.m. • Wear long-sleeved shirts, pants, hats, and sun glasses.

Inactive Ingredients

Inactive ingredients Aloe Barbadensis Leaf *, Arachidyl Alcohol, Arachidyl Glucoside, Behenyl Alcohol, Bisabolol*, Butyloctyl Salicylate, Butyrospermum Parkii (Shea) Butter*, Caprylhydroxamic Acid, Capryloyl Glycerin/Sebacic Acid Copolymer, Caprylyl Glycol, Cellulose Gum, Cetearyl Alcohol, Cetyl Alcohol, Citric Acid, Coco-Glucoside, Cocos Nucifera (Coconut) Oil, Diheptyl Succinate, Glycerin, Microcrystalline Cellulose, Polyhydroxystearic Acid, Sodium Gluconate, Sodium Hyaluronate, Sodium Stearoyl Glutamate, Theobroma Cacao (Cocoa) Seed Butter*, Tocopherol, Water.

*Indicates Certified Organic

Other information Protect this product from excessive heat and direct sun.

Questions or Comments?

1-866-326-5477

ECO

LIPS

ZINC

SPF 30

BROAD SPECTRUM SPF 30

SUNSCREEN LOTION

UNSCENTED

NON-GREASY

WATER RESISTANT

(80 MINUTES)

Moisturizer with Aloe,

Shea Butter, and Cocoa Butter.

OXYBENZONE FREE

MANUFACTURED FOR

ECO LIPS, INC.

CEDAR RAPIDS, IA 52402

ECOLIPS.COM